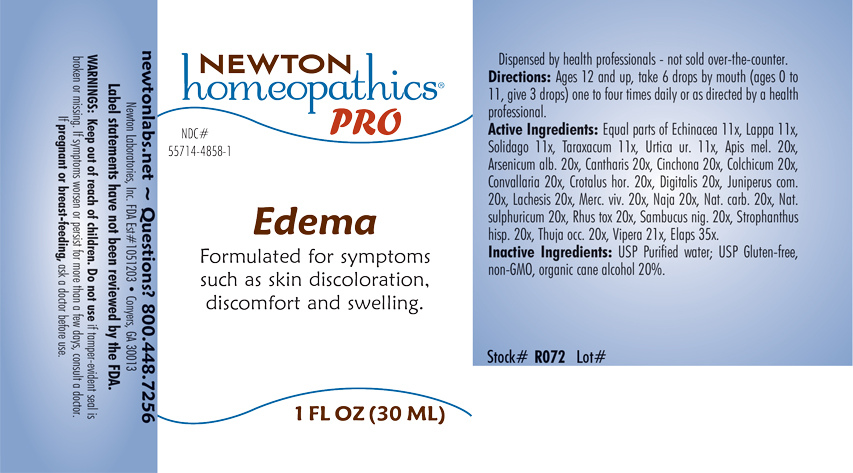 DRUG LABEL: Edema
NDC: 55714-4858 | Form: LIQUID
Manufacturer: Newton Laboratories, Inc.
Category: homeopathic | Type: HUMAN OTC DRUG LABEL
Date: 20240326

ACTIVE INGREDIENTS: MICRURUS CORALLINUS VENOM 35 [hp_X]/1 mL; APIS MELLIFERA 20 [hp_X]/1 mL; ARSENIC TRIOXIDE 20 [hp_X]/1 mL; LYTTA VESICATORIA 20 [hp_X]/1 mL; CINCHONA OFFICINALIS BARK 20 [hp_X]/1 mL; COLCHICUM AUTUMNALE BULB 20 [hp_X]/1 mL; CONVALLARIA MAJALIS 20 [hp_X]/1 mL; CROTALUS HORRIDUS HORRIDUS VENOM 20 [hp_X]/1 mL; NAJA NAJA VENOM 20 [hp_X]/1 mL; DIGITALIS 20 [hp_X]/1 mL; LACHESIS MUTA VENOM 20 [hp_X]/1 mL; MERCURY 20 [hp_X]/1 mL; SODIUM CARBONATE 20 [hp_X]/1 mL; SODIUM SULFATE 20 [hp_X]/1 mL; TOXICODENDRON PUBESCENS LEAF 20 [hp_X]/1 mL; SAMBUCUS NIGRA FLOWERING TOP 20 [hp_X]/1 mL; STROPHANTHUS HISPIDUS SEED 20 [hp_X]/1 mL; THUJA OCCIDENTALIS LEAFY TWIG 20 [hp_X]/1 mL; VIPERA BERUS VENOM 21 [hp_X]/1 mL; ECHINACEA, UNSPECIFIED 11 [hp_X]/1 mL; ARCTIUM LAPPA ROOT 11 [hp_X]/1 mL; SOLIDAGO VIRGAUREA FLOWERING TOP 11 [hp_X]/1 mL; TARAXACUM OFFICINALE 11 [hp_X]/1 mL; URTICA URENS 11 [hp_X]/1 mL; JUNIPER BERRY 20 [hp_X]/1 mL
INACTIVE INGREDIENTS: WATER; ALCOHOL

Edema 4858L

INDICATIONS & USAGE SECTION

Formulated for smptoms such as skin discoloration, discomfort and swelling.

DOSAGE & ADMINISTRATION SECTION

Directions: Ages 12 and up, take 6 drops by mouth (ages 0 to 11, give 3 drops) one to four times daily or as directed by a health professional.

OTC - ACTIVE INGREDIENT SECTION

Equal parts of Echinacea 11x, Lappa 11x, Solidago 11x, Taraxacum 11x, Urtica ur. 11x, Apis mel. 20x, Arsenicum alb. 20x, Cantharis 20x, Cinchona 20x, Colchicum 20x, Convallaria 20x, Crotalus hor. 20x, Digitalis 20x, Juniperus com. 20x, Lachesis 20x, Merc. viv. 20x, Naja 20x, Nat. carb. 20x, Nat.sulphuricum 20x, Rhus tox 20x, Sambucus nig. 20x, Strophanthus hisp. 20x, Thuja occ. 20x, Vipera 21x, Elaps 35x.

OTC - PURPOSE SECTION

Formulated for symptoms such as skin discoloration, discomfort and swelling.

INACTIVE INGREDIENT SECTION

Inactive Ingredients: USP Purified Water; USP Gluten-free, non-GMO, organic cane alcohol 20%.

QUESTIONS SECTION

newtonlabs.net - Questions? 800.448.7256

Newton Laboratories, Inc. FDA Est # 1051203 - Conyers, GA 30013

WARNINGS SECTION

WARNINGS: Keep out of reach of children. Do not use if tamper-evident seal is broken or missing. If symptoms worsen or persist for more than a few days, consult a doctor. If pregnant or breast-feeding, ask a doctor before use.

OTC - PREGNANCY OR BREAST FEEDING SECTION

If pregnant or breast-feeding, ask a doctor before use.

OTC - KEEP OUT OF REACH OF CHILDREN SECTION

Keep out of reach of children.